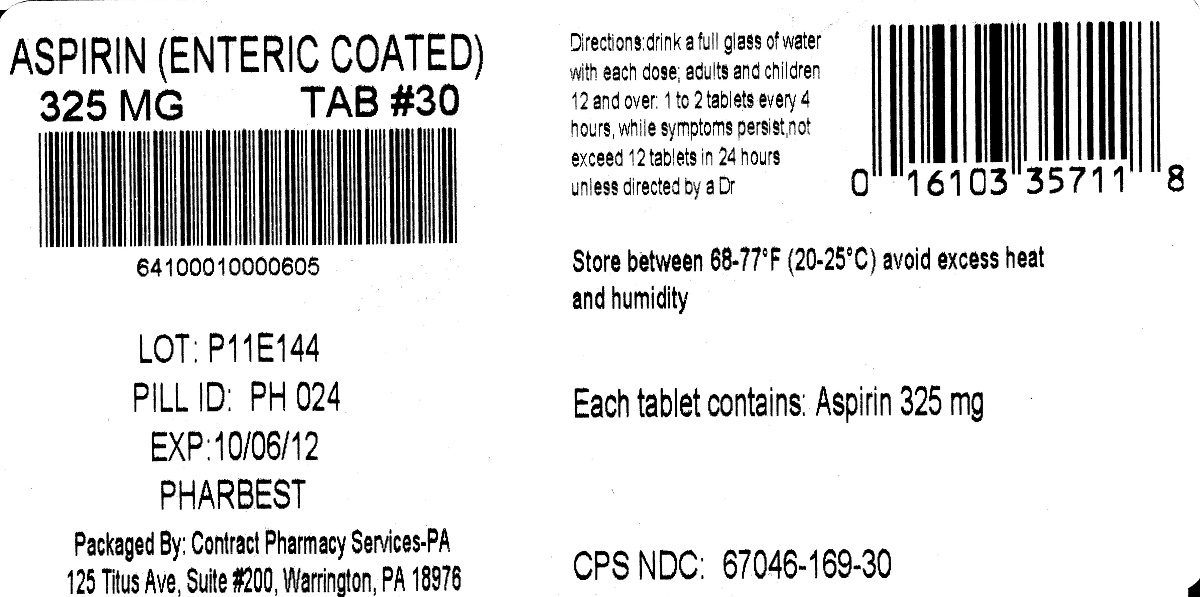 DRUG LABEL: Pharbest Aspirin 325mg
NDC: 67046-169 | Form: TABLET, DELAYED RELEASE
Manufacturer: Contract Pharmacy Services-PA
Category: otc | Type: HUMAN OTC DRUG LABEL
Date: 20170922

ACTIVE INGREDIENTS: ASPIRIN 325 mg/1 1
INACTIVE INGREDIENTS: CROSCARMELLOSE SODIUM; D&C YELLOW NO. 10; D&C RED NO. 6; HYPROMELLOSES; METHACRYLIC ACID - METHYL METHACRYLATE COPOLYMER (1:1); CELLULOSE, MICROCRYSTALLINE; POLYETHYLENE GLYCOL 400; PROPYLENE GLYCOL; SODIUM LAURYL SULFATE; STARCH, CORN; STEARIC ACID; TALC; TITANIUM DIOXIDE; TRIACETIN

169 Aspirin Enteric Coated 325 mg
Drug Facts

Active ingredient (in each tablet)

Aspirin 325mg (NSAID)*

*nonsteroidal anti-inflammatory drug

Purpose

Pain reliever

Uses

- temporarily relieves minor aches and pains due to • colds • headache • muscle pain • menstrual pain • minor pains of arthritis • toothache
- or as receommended by your doctor

Warnings

Reye's syndrome: Children and teenagers who have or are recovering from chicken pox or flu-like symptoms should not use this product. When using this product, if changes in behavior with nausea and vomiting occur, consult a doctor because these symptoms could be an early sign of Reye's syndrome, a rare but serious illness.

Allergy alert: Aspirin may cause a severe allergic reaction which may include

- hives
- facial swelling
- asthma (wheezing)
- shock

Stomach bleeding warning: This product contains a nonsteroidal anti-inflammatory drug (NSAID), which may cause severe stomach bleeding. The chance is higher if you

- are age 60 or older
- take a blood thinning (anticoagulant) or steroid drug
- take other drugs containing prescription or nonprescription NSAIDs (aspirin, ibuprofen, naproxen, or others)
- take more or for a longer time than directed
- have had stomach ulcers or bleeding problems
- have 3 or more alcoholic drinks every day while using this product

Do not use

if you have ever had an allergic reaction to aspirin or any other pain reliever/fever reducer.

Ask a doctor before use if

- stomach bleeding warning applies to you
- you have a history of stomach problems, such as heartburn
- you are taking a diuretic
- you have asthma
- you have high blood pressure, heart disease, liver cirrhosis or kidney disease

Ask a doctor or pharmacist before use if you are

taking a prescription drug for

- gout
- diabetes
- arthritis

Stop use and ask a doctor if

- an allergic reaction occurs. Seek medical help right away.
- you experience any of the following signs of stomach bleeding •feel faint • vomit blood • have bloody or black stools
- have stomach pain that does not get better
- pain gets worse or lasts more than 10 days
- redness or swelling is present
- any new symptoms occur
- ringing in the ears or loss of hearing occurs

These could be signs of a serious condition.

If pregnant or breast-feeding

ask a health professional before use. It is especially important not to use aspirin during the last 3 months of pregnancy unless definitely directed to do so by a doctor because it may cause problems in the unborn child or complications during delivery.

Keep out of reach of children.

In case of accidental overdose, get medical help or contact a Poison Control Center right away.

Directions

- drink a full glass of water with each dose

adults and children 12 years and over | take 1 to 2 tablets every 4 hours while symptoms persist. Do not exceed 12 tablets in 24 hours unless diretced by a physician.
children under 12 years | consult a physician

Other information

- avoid excess heat and moisture
- store below 25^0 C (77^0 F)

Inactive ingredients

croscarmellose sodium, D&C yellow #10 Lake, FD&C red #6, hypromellose, methacrylic acid copolymer, microcrystalline cellulose, polyethylene glycol, propylene glycol, sodium lauryl sulfate, starch, stearic acid, talc, titanium dioxide, triacetin.

Questions or comments?

Adverse drug event call: 1-866-562-2756

PACKAGE LABEL

Manufactured in the U.S.A

PHARBEST

Aspirin Regimen

†Compare to the active ingredient in Ecotrin® Regular Strength

#1 Choise of Cardiologists

Aspirin 325mg

Regular Strength

Safety Coated Aspirin 325mg

PAIN RELIEVER (NSAID)

NOT FOR HOUSEHOLDS WITH YOUNG CHILDREN